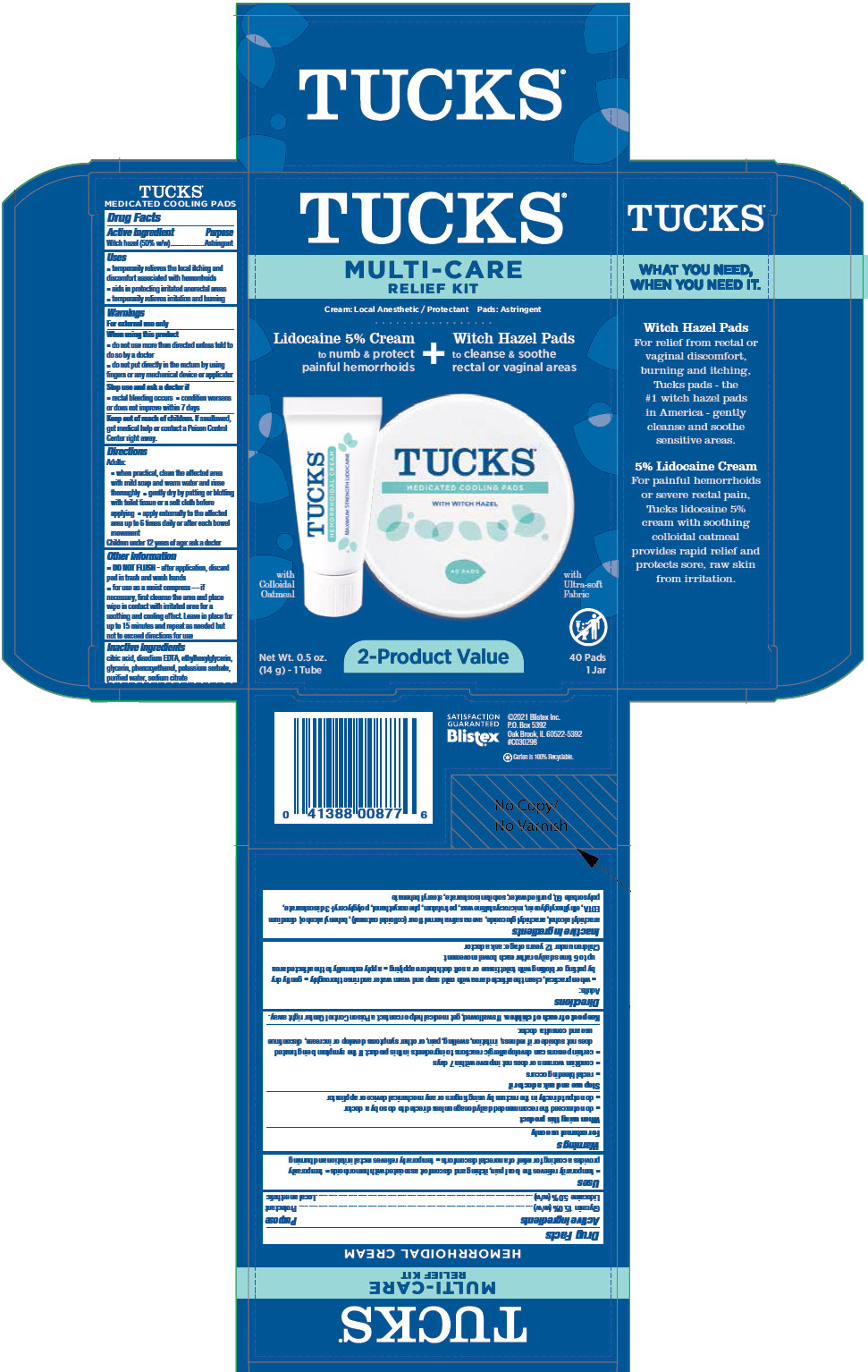 DRUG LABEL: Tucks Multi-Care Relief Kit (Tucks Hemorrhoidal and Tucks Medicated Cooling 40 Count)
NDC: 10157-2112 | Form: KIT | Route: TOPICAL
Manufacturer: Blistex Inc
Category: otc | Type: HUMAN OTC DRUG LABEL
Date: 20241213

ACTIVE INGREDIENTS: GLYCERIN 15 g/100 g; LIDOCAINE 5 g/100 g; WITCH HAZEL 500 mg/1 mL
INACTIVE INGREDIENTS: WATER; PETROLATUM; MICROCRYSTALLINE WAX; STEARYL BEHENATE; SORBITAN ISOSTEARATE; POLYSORBATE 60; ARACHIDYL ALCOHOL; DOCOSANOL; ARACHIDYL GLUCOSIDE; POLYGLYCERYL-3 DIISOSTEARATE; OATMEAL; PHENOXYETHANOL; ETHYLHEXYLGLYCERIN; EDETATE DISODIUM ANHYDROUS; WATER; GLYCERIN; PROPYLENE GLYCOL; DIAZOLIDINYL UREA; METHYLPARABEN; PROPYLPARABEN; SODIUM CITRATE, UNSPECIFIED FORM; CITRIC ACID MONOHYDRATE

Tucks® Multi-Care Relief Kit (Tucks® Hemorrhoidal Cream and Tucks® Medicated Cooling Pads 40 Count)

Tucks® Hemorrhoidal Cream

Drug Facts

ACTIVE INGREDIENT

Active ingredients | Purpose
Glycerin 15.0% (w/w) | Protectant
Lidocaine 5.0% (w/w) | Local anesthetic

Uses

- temporarily relieves the local pain, itching and discomfort associated with hemorrhoids
- temporarily provides a coating for relief of anorectal discomforts
- temporarily relieves rectal irritation and burning

Warnings

For external use only

When using this product

- do not exceed the recommended daily dosage unless directed to do so by a doctor
- do not put directly in the rectum by using fingers or any mechanical device or applicator

Stop use and ask a doctor if

- rectal bleeding occurs
- condition worsens or does not improve within 7 days
- certain persons can develop allergic reactions to ingredients in this product. If the symptom being treated does not subside or if redness, irritation, swelling, pain, or other symptoms develop or increase, discontinue use and consult a doctor.

Keep out of reach of children. If swallowed, get medical help or contact a Poison Control Center right away.

Directions

Adults:

- when practical, clean the affected area with mild soap and warm water and rinse thoroughly 
- gently dry by patting or blotting with toilet tissue or a soft cloth before applying
- apply externally to the affected area up to 6 times daily or after each bowel movement

Children under 12 years of age: ask a doctor

Inactive ingredients

arachidyl alcohol, arachidyl glucoside, avena sativa kernel flour (colloidal oatmeal), behenyl alcohol, disodium EDTA, ethylhexylglycerin, microcrystalline wax, petrolatum, phenoxyethanol, polyglyceryl-3 diisostearate, polysorbate 60, purified water, sorbitan isostearate, stearyl behenate

Tucks® Medicated Cooling Pads

Drug Facts

Active ingredient

Witch hazel (50% w/w)

Purpose

Astringent

Uses

- temporarily relieves the local itching and discomfort associated with hemorrhoids
- aids in protecting irritated anorectal areas
- temporarily relieves irritation and burning

Warnings

For external use only

When using this product

- do not use more than directed unless told to do so by a doctor
- do not put directly in the rectum by using fingers or any mechanical device or applicator

Stop use and ask a doctor if

- rectal bleeding occurs
- condition worsens or does not improve within 7 days

Keep out of reach of children. If swallowed, get medical help or contact a Poison Control Center right away.

Directions

Adults:

- when practical, clean the affected area with mild soap and warm water and rinse thoroughly
- gently dry by patting or blotting with toilet tissue or a soft cloth before applying
- apply externally to the affected area up to 6 times daily or after each bowel movement

Children under 12 years of age: ask a doctor

Other information

- DO NOT FLUSH - after application, discard pad in trash and wash hands
- for use as a moist compress — if necessary, first cleanse the area and place wipe in contact with irritated area for a soothing and cooling effect. Leave in place for up to 15 minutes and repeat as needed but not to exceed directions for use

Inactive ingredients

citric acid, disodium EDTA, ethylhexylglycerin, glycerin, phenoxyethanol, potassium sorbate, purified water, sodium citrate

PRINCIPAL DISPLAY PANEL - Kit Carton

TUCKS®

MULTI-CARE
RELIEF KIT

Cream: Local Anesthetic / Protectant
Pads: Astringent

Lidocaine 5% Cream
to numb & protect
painful hemorrhoids
+
Witch Hazel Pads
to cleanse & soothe
rectal or vaginal areas

TUCKS®
HEMORRHOIDAL CREAM
MAXIMUM STRENGTH LIDOCAINE

with
Colloidal
Oatmeal

TUCKS®
MEDICATED COOLING PADS
WITH WITCH HAZEL
40 PADS

with
Ultra-soft
Fabric

Net Wt. 0.5 oz.
(14 g) - 1 Tube

2-Product Value

40 Pads
1 Jar